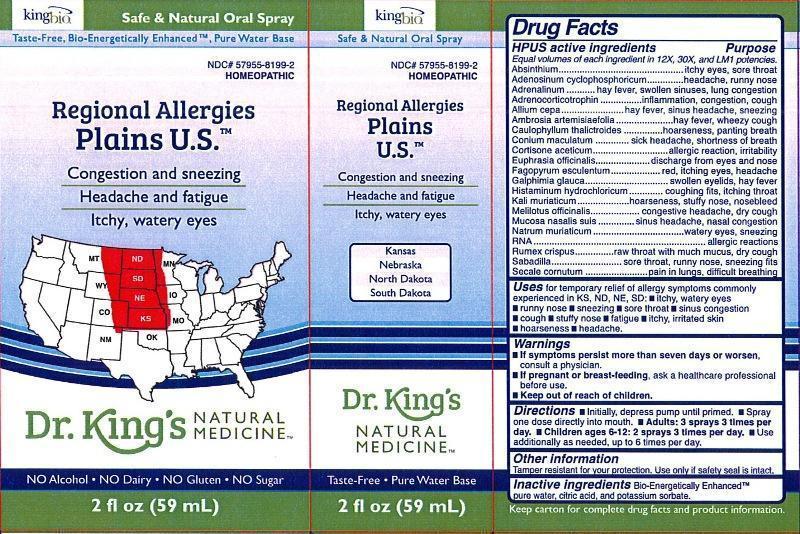 DRUG LABEL: Regional Allergies Plains U.S.
NDC: 57955-8199 | Form: LIQUID
Manufacturer: King Bio Inc.
Category: homeopathic | Type: HUMAN OTC DRUG LABEL
Date: 20130925

ACTIVE INGREDIENTS: WORMWOOD 12 [hp_X]/59 mL; ADENOSINE CYCLIC PHOSPHATE 12 [hp_X]/59 mL; EPINEPHRINE 12 [hp_X]/59 mL; CORTICOTROPIN 12 [hp_X]/59 mL; ONION 12 [hp_X]/59 mL; AMBROSIA ARTEMISIIFOLIA 12 [hp_X]/59 mL; CAULOPHYLLUM THALICTROIDES ROOT 12 [hp_X]/59 mL; CONIUM MACULATUM FLOWERING TOP 12 [hp_X]/59 mL; CORTISONE ACETATE 12 [hp_X]/59 mL; EUPHRASIA STRICTA 12 [hp_X]/59 mL; FAGOPYRUM ESCULENTUM 12 [hp_X]/59 mL; GALPHIMIA GLAUCA FLOWERING TOP 12 [hp_X]/59 mL; HISTAMINE DIHYDROCHLORIDE 12 [hp_X]/59 mL; POTASSIUM CHLORIDE 12 [hp_X]/59 mL; MELILOTUS OFFICINALIS TOP 12 [hp_X]/59 mL; SUS SCROFA NASAL MUCOSA 12 [hp_X]/59 mL; SODIUM CHLORIDE 12 [hp_X]/59 mL; SACCHAROMYCES CEREVISIAE RNA 12 [hp_X]/59 mL; RUMEX CRISPUS ROOT 12 [hp_X]/59 mL; SCHOENOCAULON OFFICINALE SEED 12 [hp_X]/59 mL; CLAVICEPS PURPUREA SCLEROTIUM 12 [hp_X]/59 mL
INACTIVE INGREDIENTS: WATER; CITRIC ACID MONOHYDRATE; POTASSIUM SORBATE

Regional Allergies Plains U.S.™

Drug Facts

____________________________________________________________________________________________________________

HPUS active ingredients: Absinthium, Adenosinum cyclophosphoricum, Adrenalinum, Adrenocorticotrophin, Allium cepa, Ambrosia artemisiaefolia, Caulophyllum thalictroides, Conium maculatum, Cortisone aceticum, Euphrasia officinalis, Fagopyrum esculentum, Galphimia glauca, Histaminum hydrochloricum, Kali muriaticum, Melilotus officinalis, Mucosa nasalis suis, Natrum muriaticum, RNA, Rumex crispus, Sabadilla, Secale cornutum.

INDICATIONS AND USAGE

Uses for temporary relief of allergy symptoms commonly experienced in KS, ND, NE, SD:

- itchy, watery eyes
- runny nose
- sneezing
- sore throat
- sinus congestion
- cough
- stuffy nose
- fatigue
- itchy, irritated skin
- hoarseness
- headache

Warnings

- If symptoms persist more than seven days or worsen, consult a physician.
- If pregnant or breast-feeding, ask a healthcare professional before use.

- Keep out of reach of children.

Directions:

- Initially, depress pump until primed.
- Spray one dose directly into mouth.
- Adults: 3 sprays 3 times per day.
- Children 6-12 years: 2 sprays 3 times per day.
- Use additionally as needed, up to 6 times per day.

OTHER SAFETY INFORMATION

Tamper resistant for your protection. Use only if safety seal is intact.

INACTIVE INGREDIENT

Inactive Ingredients: Bio-Energetically Enhanced™ pure water, citric acid and potassium sorbate.

Drug Facts

__________________________________________________________________________________________________________________

HPUS active ingredients Purpose

Equal volumes of each ingredient in 12X, 30X, and LM1 potencies.

Absinthium.............................................................................itchy eyes, sore throat

Adenosinum cyclophosphoricum................................................headache, runny nose

Adrenalinum...........................................................................hay fever, swollen sinuses, lung congestion

Adrenocorticotrophin................................................................inflammation, congestion, cough

Allium cepa.............................................................................hay fever, sinus headache, sneezing

Ambrosia artemisiaefolia...........................................................hay fever, wheezy cough

Caulopyllum thalictroides..........................................................hoarseness, panting breath

Conium maculatum..................................................................sick headache, shortness of breath

Cortisone aceticum.................................................................allergic reaction, irritability

Euphrasia officinalis.................................................................discharge from eyes and nose

Fagopyrum esculentum............................................................red, itching eyes, headache

Galphimia glauca.....................................................................swollen eyelids, hay fever

Histaminum hydrochloricum......................................................coughing fits, itching throat

Kali muriaticum.......................................................................hoarseness, stuffy nose, nosebleed

Melilotus officinalis...................................................................congestive headache, dry cough

Mucosa nasalis suis..................................................................sinus headache, nasal congestion

Natrum muriaticum..................................................................watery eyes, sneezing

RNA.......................................................................................allergic reactions

Rumex crispus.........................................................................raw throat with much mucus, dry cough

Sabadilla.................................................................................sore throat, runny nose, sneezing fits

Secale cornutum......................................................................pain in lungs, difficult breathing